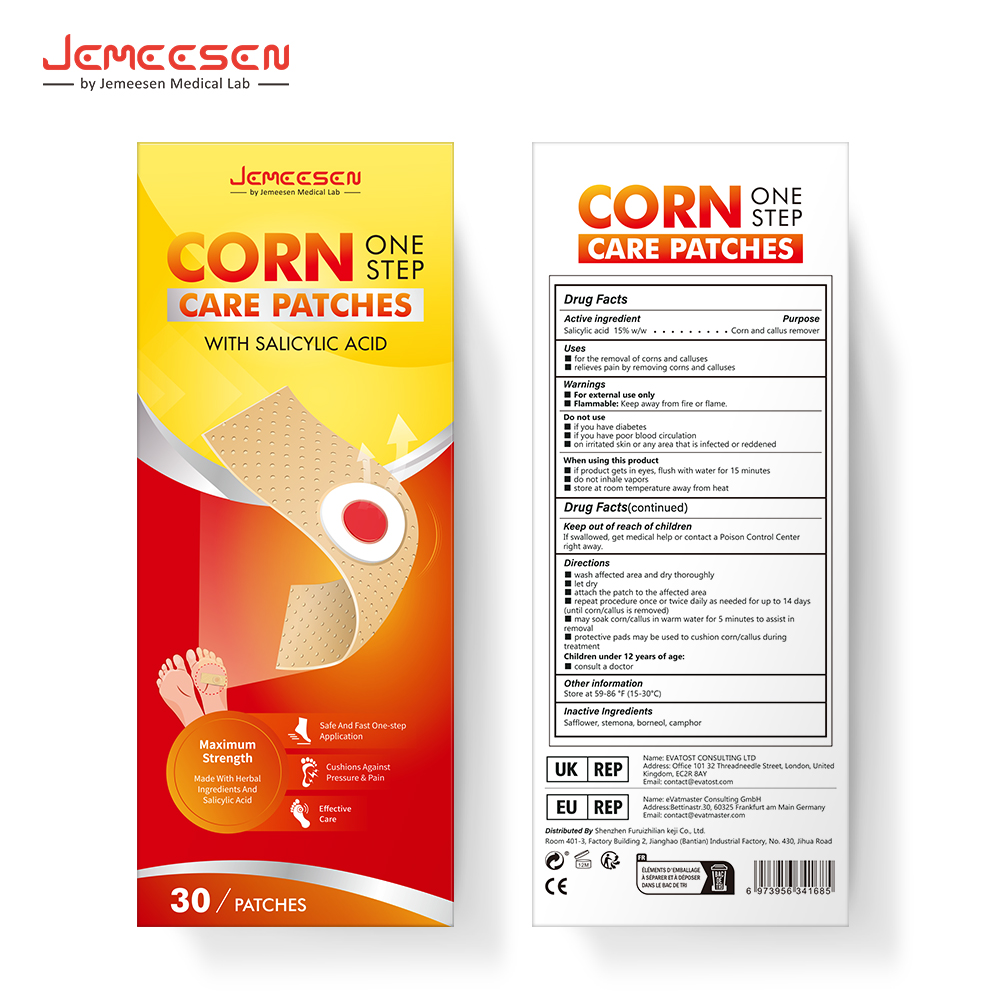 DRUG LABEL: CORN CARE PATCHES
NDC: 84445-011 | Form: PATCH
Manufacturer: Shenzhen Furuizhilian keji Co., Ltd.
Category: otc | Type: HUMAN OTC DRUG LABEL
Date: 20240808

ACTIVE INGREDIENTS: SALICYLIC ACID 1.5 g/30 1
INACTIVE INGREDIENTS: CAMPHOR, (-)-; SAFFLOWER; STEMONA TUBEROSA ROOT; BORNEOL

ACTIVE INGREDIENT

Salicylic acid 15%

INDICATIONS AND USAGE

■ for the removal of corns and calluses
■ relieves pain by removing corns and calluses

WARNINGS

■ For external use only

■ Flammable: Keep away from fire or flame.

DO NOT USE

■ if you have diabetes
■ if you have poor blood circulation
■ on irritated skin or any area that is infected or reddened

WHEN USING

■ if product gets in eyes, flush with water for 15 minutes
■ do not inhale vapors
■ store at room temperature away from heat

STOP USE

discomfort lasts

KEEP OUT OF REACH OF CHILDREN

If swallowed, get medical help or contact a Poison Control Center right away.

DOSAGE AND ADMINISTRATION

■ wash affected area and dry thoroughly
■ let dry
■ attach the patch to the affected area
■ repeat procedure once or twice daily as needed for up to 14 days (until corn/callus is removed)
■ may soak corn/callus in warm water for 5 minutes to assist in removal
■ protective pads may be used to cushion corn/callus during treatment
Children under 12 years of age:
consult a doctor

INACTIVE INGREDIENT

safflower, stemona, borneol, camphor

PURPOSE

Corn and callus remover